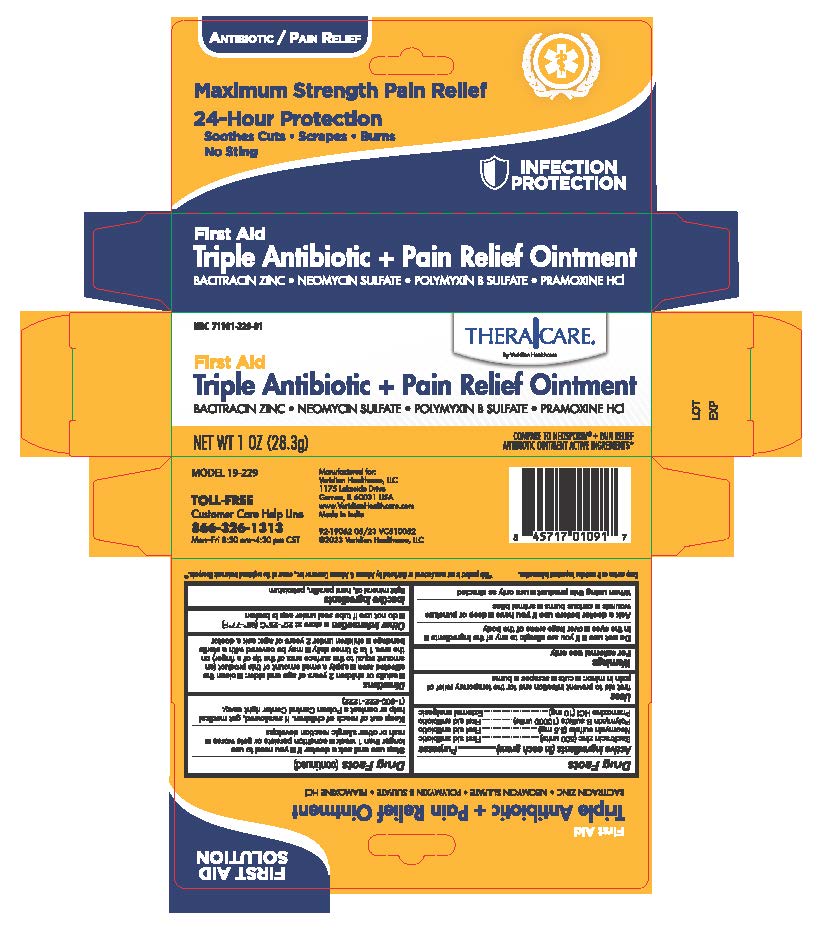 DRUG LABEL: TheraCare Triple Antibiotic Pain Relief
NDC: 71101-229 | Form: OINTMENT
Manufacturer: Veridian Healthcare
Category: otc | Type: HUMAN OTC DRUG LABEL
Date: 20251002

ACTIVE INGREDIENTS: BACITRACIN ZINC 500 [USP'U]/1 g; NEOMYCIN SULFATE 3.5 mg/1 g; PRAMOXINE HYDROCHLORIDE 10 mg/1 g; POLYMYXIN B SULFATE 10000 [USP'U]/1 g
INACTIVE INGREDIENTS: PETROLATUM; LIGHT MINERAL OIL; PARAFFIN

TheraCare Triple Antibiotic Pain relief Ointment

Active Ingredient

Bacitracin zinc 500 Units

Neomycin sulfate (3.5mg)

Polymyxin B sulfate (10000 units)

Pramoxine HCI (10mg)

Purpose

First Aid Antibiotic

external analgesic

Uses

First Aid to help prevent infection and for temporary relief of pain in minor:

- Cuts
- Scrapes
- Burns

Warnings

For external use only.

Do not use

If you are allergic to any of the ingredients
In eyes
Over large areas of the body

Ask a Doctor before Use

Ask Doctor before use if you have:

- Deep or puncture wouns
- Animal bites
- Serious burns

When using this product

use only as directed

Stop Use and ask a Doctor if:

- You need to use longer than 1 week
- Condition persists or gets worse
- rash or other allergic reaction develops

Keep out of Reach of Children

If Swallowed, get medical help or contact a Poison Control Center right away (1-800-222-1222).

Directions

- adults or children 2 years of age and older:
- Clean the affected area
- Apply a small amount of this product (an amount equal to the surface area of the tip of a finger) on the area 1 to 3 times daily
- May be covered with a sterile bandage
- Children under 2 years of age: ask doctor

Other Information

- Store at 20° to 25°C (68° to 77°F)
- do not use if tube seal under cap is broken

Inactive Ingredient:

Light mineral oil, hard paraffin, Petrolatum

Questions?

Call 866-326-1313